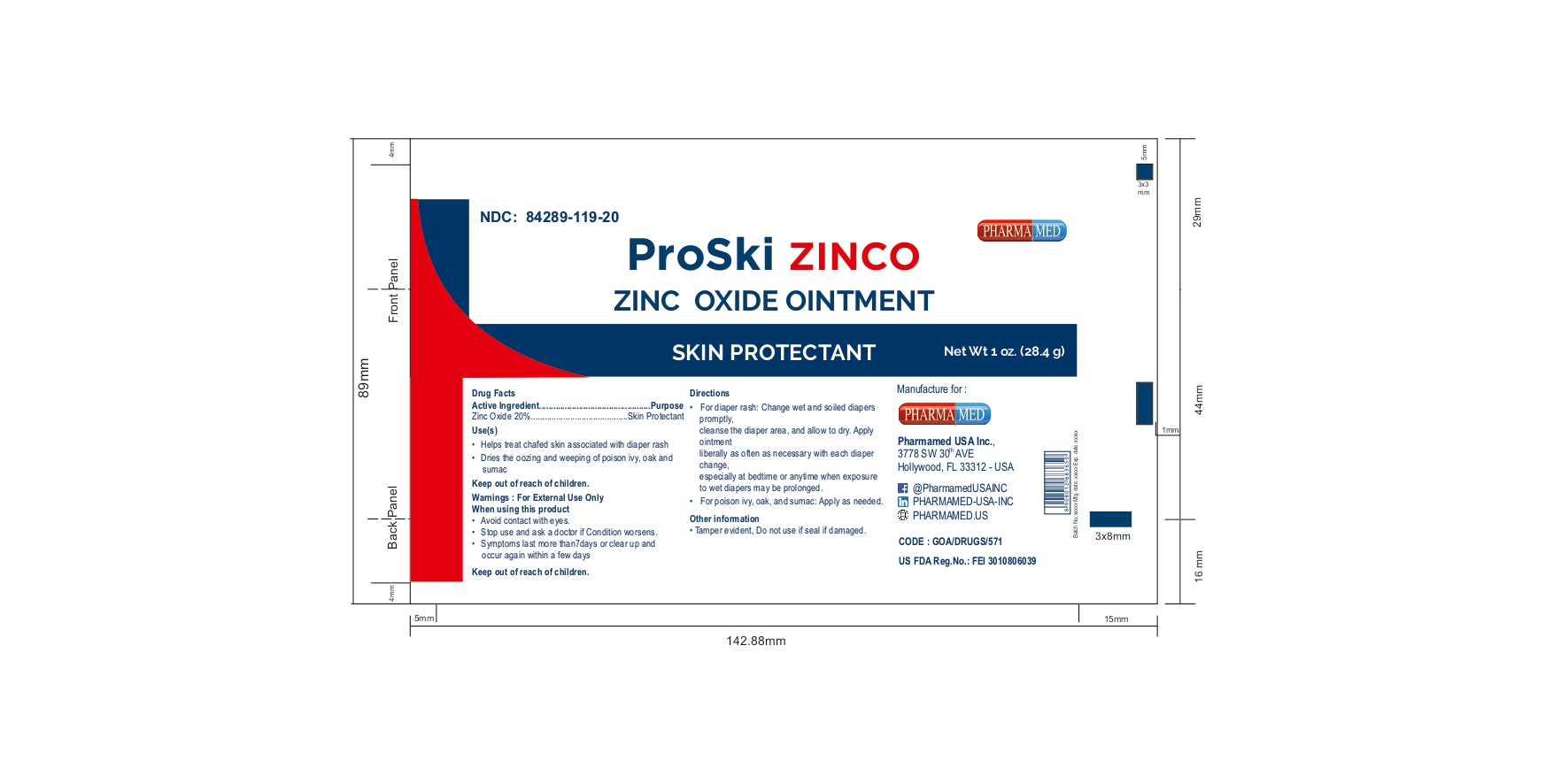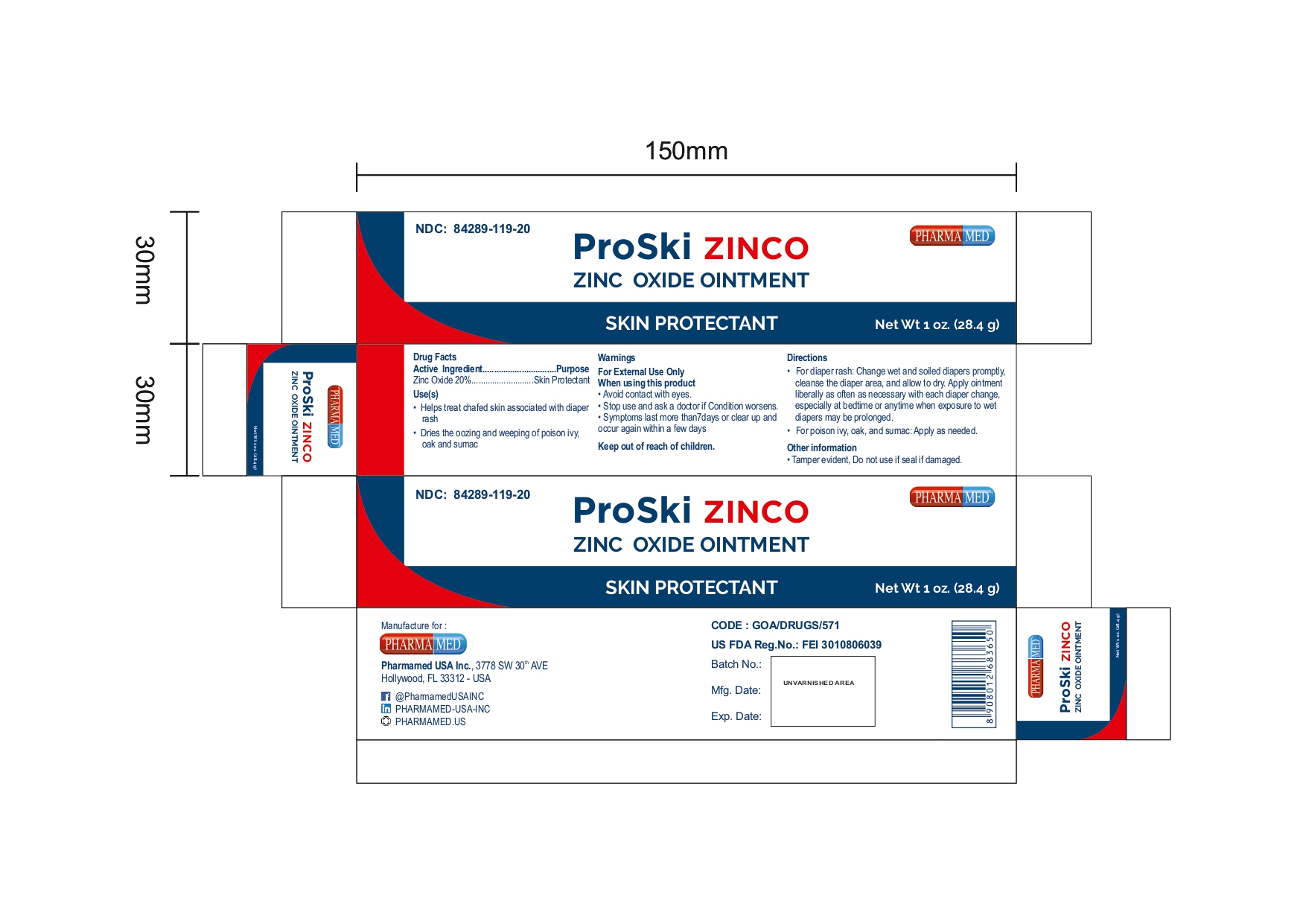 DRUG LABEL: PROSKI ZINCO SKIN PROTECTANT
NDC: 84289-119 | Form: OINTMENT
Manufacturer: PHARMAMED USA INC
Category: otc | Type: HUMAN OTC DRUG LABEL
Date: 20250318

ACTIVE INGREDIENTS: ZINC OXIDE 200 mg/1 g
INACTIVE INGREDIENTS: CETETH-20; LIGHT MINERAL OIL; CETOSTEARYL ALCOHOL; WHITE PETROLATUM

Zinc Oxide Ointment

ACTIVE INGREDIENT

Zinc Oxide 20%

PURPOSE

Skin Protectant

USE

Helps treat chafed skin associated with diaper rash

Dries the oozing and weeping of poison: • ivy • oak •sumac

WARNINGS

For External Use Only.

When using this product

- Avoid contact with eyes

Stop use and ask a doctor if

- Condition worsens
- Symptoms last more than 7 days or clear up and occur again within a few days

Keep out of reach of children

If swallowed, get medical help or contact a Poison Control Center (1-800-222-1222) right away

DIRECTIONS

• For diaper rash: Change wet and soiled diapers promptly, cleanse the diaper area,

and allow to dry.

• Apply ointment liberally as often as necessary with each diaper

change, especially at bedtime or anytime when exposure to wet diapers may be

prolonged.

• For poison ivy, oak, and sumac: Apply as needed.

OTHER INFORMATION

- Store at room temperature between 15º - 30ºC (59º - 86ºF)
- Avoid excessive heat
- Tamper evident. Do not use if seal is damaged.

INACTIVE INGREDIENTS

CETETH-20, CETOSTEARYL ALCOHOL, LIGHT MINERAL OIL, WHITE PETROLATUM

QUESTIONS OR COMMENTS?

(754)-200-8994 (Mon-Fri 8 AM to 4 PM EST)

PACKAGE/LABEL PRINCIPAL DISPLAY PANEL

NDC: 84289-119-20

ZINC OXIDE OINTMENT

Skin Protectant

Net Wt 1 oz. (28.4 g)

GOA/DRUGS/571